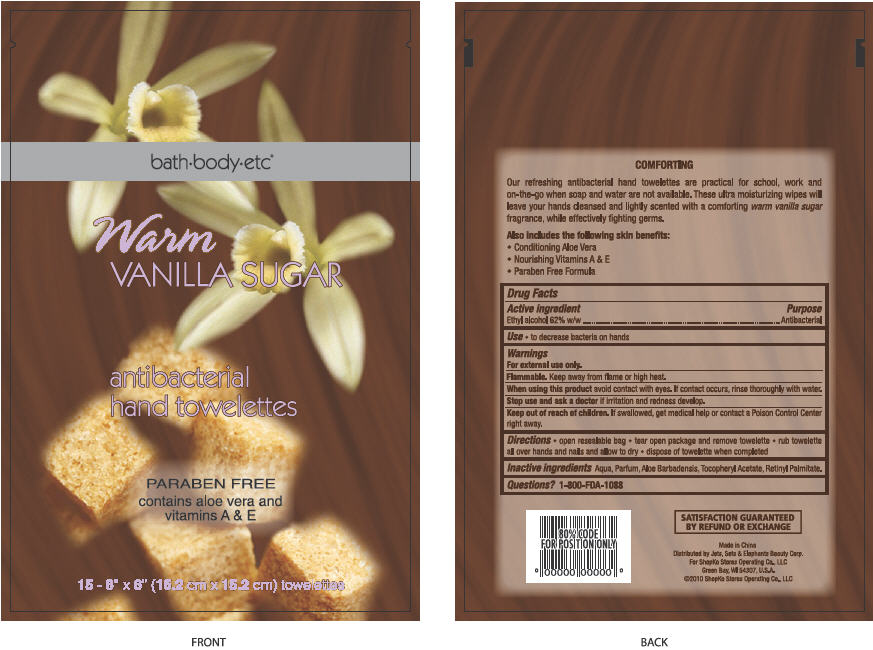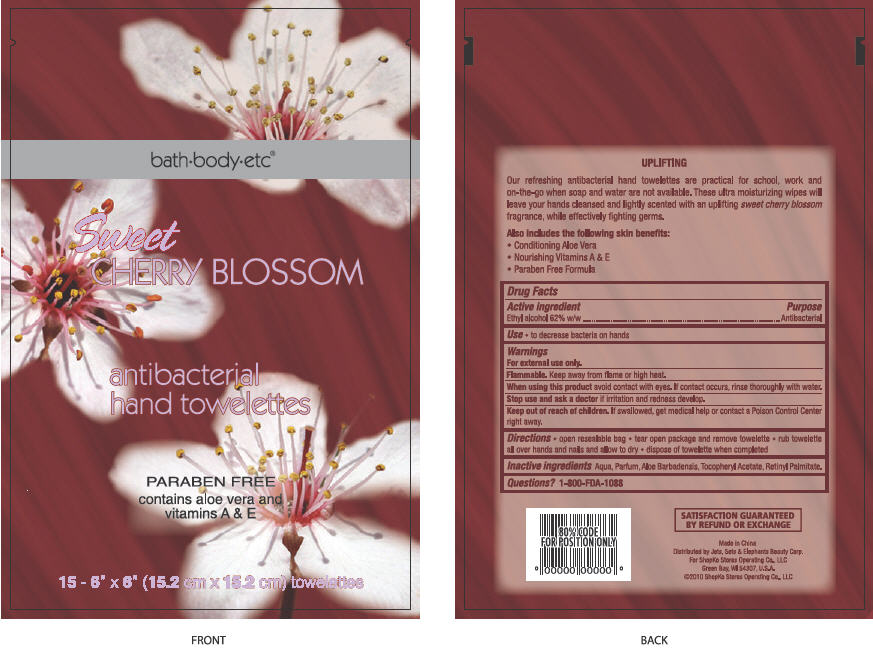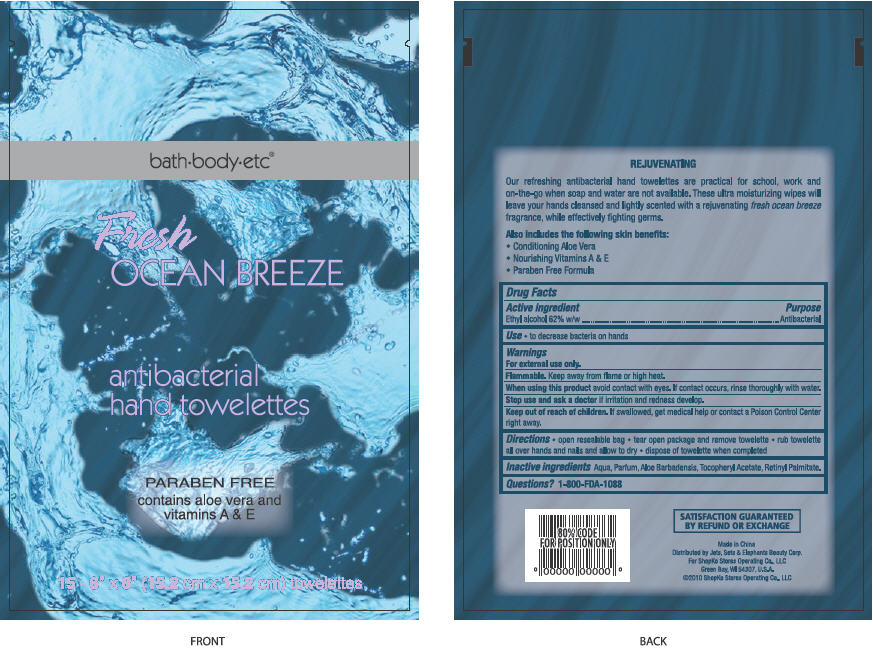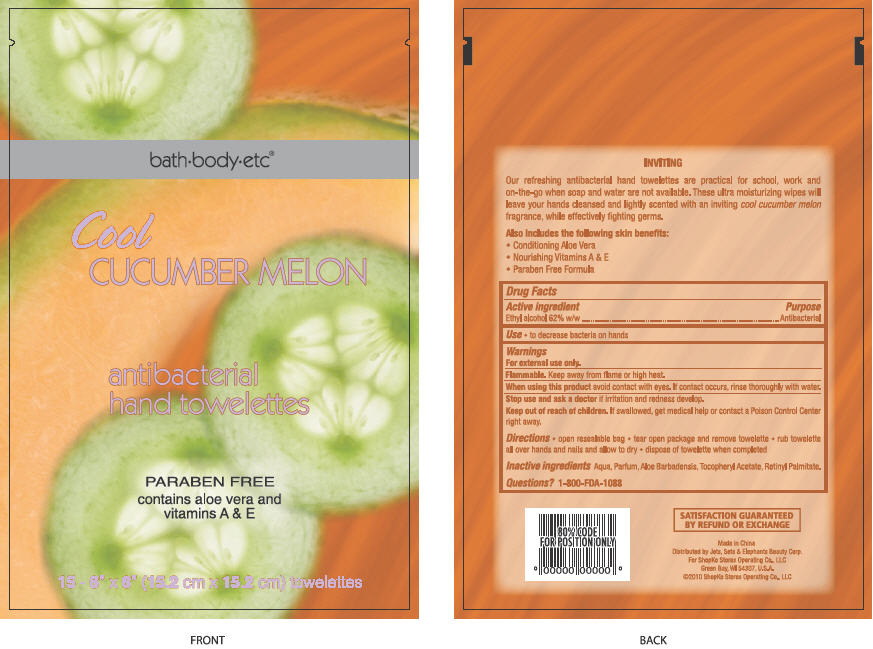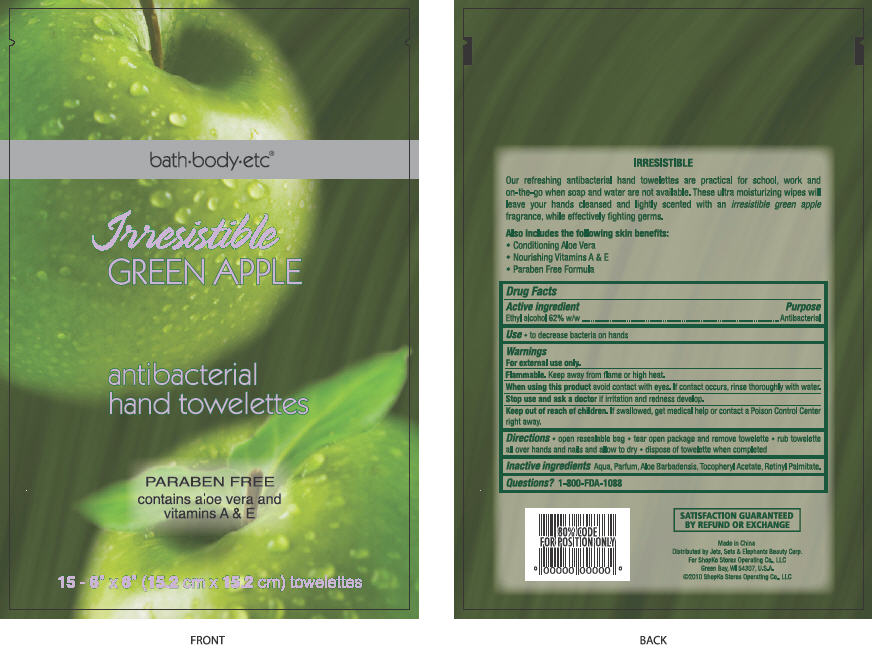 DRUG LABEL: Antibacterial Hand Towelettes
NDC: 50988-230 | Form: SWAB
Manufacturer: Jets, Sets, & Elephants Beauty Corp.
Category: otc | Type: HUMAN OTC DRUG LABEL
Date: 20100720

ACTIVE INGREDIENTS: ALCOHOL 0.62 mL/1 1
INACTIVE INGREDIENTS: WATER; ALOE VERA LEAF; .ALPHA.-TOCOPHEROL ACETATE, D-; VITAMIN A PALMITATE

bath+body+etc® antibacterial hand towelettes - Warm Vanilla Sugar, Sweet Cherry Blossom, Fresh Ocean Breeze, Cool Cucumber Melon, Irresistible Green Apple

Active ingredient

Ethyl alcohol 62% w/w

Purpose

Antibacterial

Use

- to decrease bacteria on hands

Warnings

For external use only.

Flammable. Keep away from flame or high heat.

When using this product avoid contact with the eyes. If contact occurs, rinse thoroughly with water.

Stop use and ask a doctor if irritation and redness develop.

Keep out of reach of children. If swallowed, get medical help or contact a Poison Control Center right away.

Directions

- open resealable bag
- tear open package and remove towelette
- rub towelette all over hands and nails and allow to dry
- dispose of towelette when completed

Inactive ingredients

Aqua, Parfum, Aloe Barbadensis, Tocopheryl Acetate, Retinyl Palmitate

Questions?

1-800-FDA-1088

SATISFACTION GUARANTEED BY REFUND OR EXCHANGE

Made in China

Distributed by Jets, Sets & Elephants Beauty Corp.

For Shopko Stores Operating Co., LLC

Green Bay, WI 54307, U.S.A.

©2010 Shopko Stores Operating Co., LLC

Package/Label Principal Display Panel - Bag Label

bath+body+etc®

Warm

VANILLA SUGAR

antibacterial

hand towelettes

PARABEN FREE

contains aloe vera and

vitamins A & E

15 - 6” x 6” (15.2 cm x 15.2 cm) towelettes

COMFORTING

Our refreshing antibacterial hand towelettes are practical for school, work and on-the-go when soap and water are not available. These ultra moisturizing wipes will leave your hands cleansed and lightly scented with a comforting warm vanilla sugar fragrance, while effectively fighting germs.

Also includes the following skin benefits:

- Conditioning Aloe Vera
- Nourishing Vitamins A & E
- Paraben Free Formula

Warm Vanilla Sugar Bag Label

Package/Label Principal Display Panel - Bag Label

bath+body+etc®

Sweet

CHERRY BLOSSOM

antibacterial

hand towelettes

PARABEN FREE

contains aloe vera and

vitamins A & E

15 - 6” x 6” (15.2 cm x 15.2 cm) towelettes

UPLIFTING

Our refreshing antibacterial hand towelettes are practical for school, work and on-the-go when soap and water are not available. These ultra moisturizing wipes will leave your hands cleansed and lightly scented with an uplifting sweet cherry blossom fragrance, while effectively fighting germs.

Also includes the following skin benefits:

- Conditioning Aloe Vera
- Nourishing Vitamins A & E
- Paraben Free Formula

Sweet Cherry Blossom Bag Label

Package/Label Principal Display Panel - Bag Label

bath+body+etc®

Fresh

OCEAN BREEZE

antibacterial

hand towelettes

PARABEN FREE

contains aloe vera and

vitamins A & E

15 - 6” x 6” (15.2 cm x 15.2 cm) towelettes

REJUVENATING

Our refreshing antibacterial hand towelettes are practical for school, work and on-the-go when soap and water are not available. These ultra moisturizing wipes will leave your hands cleansed and lightly scented with a rejuvenating fresh ocean breeze fragrance, while effectively fighting germs.

Also includes the following skin benefits:

- Conditioning Aloe Vera
- Nourishing Vitamins A & E
- Paraben Free Formula

Fresh Ocean Breeze Bag Label

Package/Label Principal Display Panel - Bag Label

bath+body+etc®

Cool

CUCUMBER MELON

antibacterial

hand towelettes

PARABEN FREE

contains aloe vera and

vitamins A & E

15 - 6” x 6” (15.2 cm x 15.2 cm) towelettes

INVITING

Our refreshing antibacterial hand towelettes are practical for school, work and on-the-go when soap and water are not available. These ultra moisturizing wipes will leave your hands cleansed and lightly scented with an inviting cool cucumber melon fragrance, while effectively fighting germs.

Also includes the following skin benefits:

- Conditioning Aloe Vera
- Nourishing Vitamins A & E
- Paraben Free Formula

Cool Cucumber Melon Bag Label

Package/Label Principal Display Panel - Bag Label

bath+body+etc®

Irresistible

GREEN APPLE

antibacterial

hand towelettes

PARABEN FREE

contains aloe vera and

vitamins A & E

15 - 6” x 6” (15.2 cm x 15.2 cm) towelettes

IRRESISTIBLE

Our refreshing antibacterial hand towelettes are practical for school, work and on-the-go when soap and water are not available. These ultra moisturizing wipes will leave your hands cleansed and lightly scented with an irresistible green apple fragrance, while effectively fighting germs.

Also includes the following skin benefits:

- Conditioning Aloe Vera
- Nourishing Vitamins A & E
- Paraben Free Formula

Irresistible Green Apple Bag Label